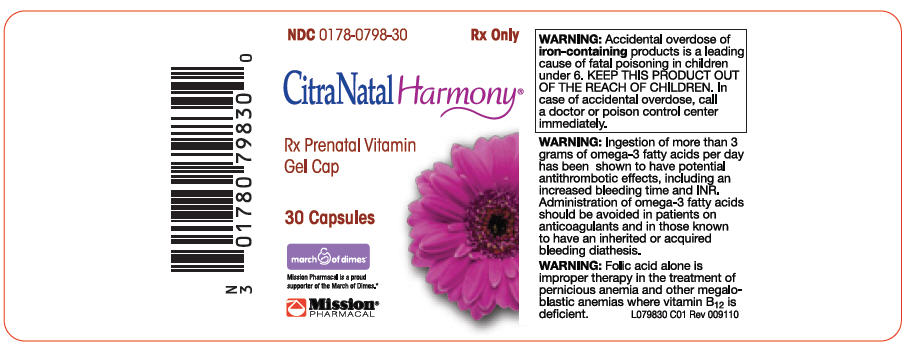 DRUG LABEL: CitraNatal Harmony
NDC: 0178-0798 | Form: CAPSULE, GELATIN COATED
Manufacturer: MISSION PHARMACAL COMPANY
Category: prescription | Type: HUMAN PRESCRIPTION DRUG LABEL
Date: 20120118

ACTIVE INGREDIENTS: Calcium citrate 104 mg/1 1; Iron pentacarbonyl 30 mg/1 1; Cholecalciferol 400 [iU]/1 1; .Alpha.-Tocopherol, Dl- 30 [iU]/1 1; Pyridoxine hydrochloride 25 mg/1 1; Folic Acid 1 mg/1 1; Docusate Sodium 50 mg/1 1; Doconexent 260 mg/1 1

CitraNatal Harmony®
Rx Prenatal Vitamin
Gel Cap

Rx Only

DESCRIPTION

CitraNatal Harmony® is a prescription prenatal/postnatal multivitamin/mineral soft gelatin capsule. The prenatal vitamin is a purple, opaque soft gelatin capsule containing a greenish-gray liquid to semi-solid fill. The capsule is printed "0798" in white ink.

Each prenatal capsule contains:

Calcium (Calcium citrate) | 104 | mg
Iron (Carbonyl iron) | 30 | mg
Vitamin D3 (Cholecalciferol) | 400 | IU
Vitamin E (dl-alpha tocopheryl acetate) | 30 | IU
Vitamin B6 (Pyridoxine HCl) | 25 | mg
Folic Acid | 1 | mg
Docusate Sodium | 50 | mg
Docosahexaenoic Acid (DHA 40% from 650 mg Algal Oil) | 260 | mg

INDICATIONS

CitraNatal Harmony® is a multivitamin/mineral prescription drug indicated for use in improving the nutritional status of women prior to conception, throughout pregnancy, and in the postnatal period for both lactating and nonlactating mothers.

CONTRAINDICATIONS

This product is contraindicated in patients with a known hypersensitivity to any of the ingredients.

WARNING

Accidental overdose of iron-containing products is a leading cause of fatal poisoning in children under 6. KEEP THIS PRODUCT OUT OF THE REACH OF CHILDREN. In case of accidental overdose, call a doctor or poison control center immediately.

WARNING

Ingestion of more than 3 grams of omega-3 fatty acids per day has been shown to have potential antithrombotic effects, including an increased bleeding time and INR. Administration of omega-3 fatty acids should be avoided in patients on anticoagulants and in those known to have an inherited or acquired bleeding diathesis.

WARNING

Folic acid alone is improper therapy in the treatment of pernicious anemia and other megaloblastic anemias where vitamin B12 is deficient.

PRECAUTIONS

Folic acid in doses above 0.1 mg daily may obscure pernicious anemia in that hematologic remission can occur while neurological manifestations progress.

ADVERSE REACTIONS

Allergic sensitization has been reported following both oral and parenteral administration of folic acid.

CAUTION: Exercise caution to ensure that the prescribed dosage of DHA does not exceed 1 gram (1000 mg) per day.

DOSAGE AND ADMINISTRATION

One capsule daily or as directed by a physician.

STORAGE AND HANDLING

Store at controlled room temperature.

NOTICE: Contact with moisture can discolor or erode the capsule.

HOW SUPPLIED

Bottles of 30 capsules each - NDC 0178-0798-30.

To report a serious adverse event or obtain product information, call (210) 696-8400.

life'sDHA™

Trademark of Martek Biosciences Corporation
U.S. Patent No. 5,407,957
U.S. Patent No. 5,492,938

Manufactured for:
MISSION PHARMACAL COMPANY
San Antonio, TX USA 78230 1355

Copyright © 2011 Mission Pharmacal Company.
All rights reserved.

MADE IN CANADA

L079830 C01 Rev 009110

PRINCIPAL DISPLAY PANEL - 30 Capsule Bottle Label

NDC 0178-0798-30

Rx Only

CitraNatal Harmony®

Rx Prenatal Vitamin
Gel Cap

30 Capsules

march of dimes®

Mission Pharmacal is a proud
supporter of the March of Dimes.*

Mission®
PHARMACAL